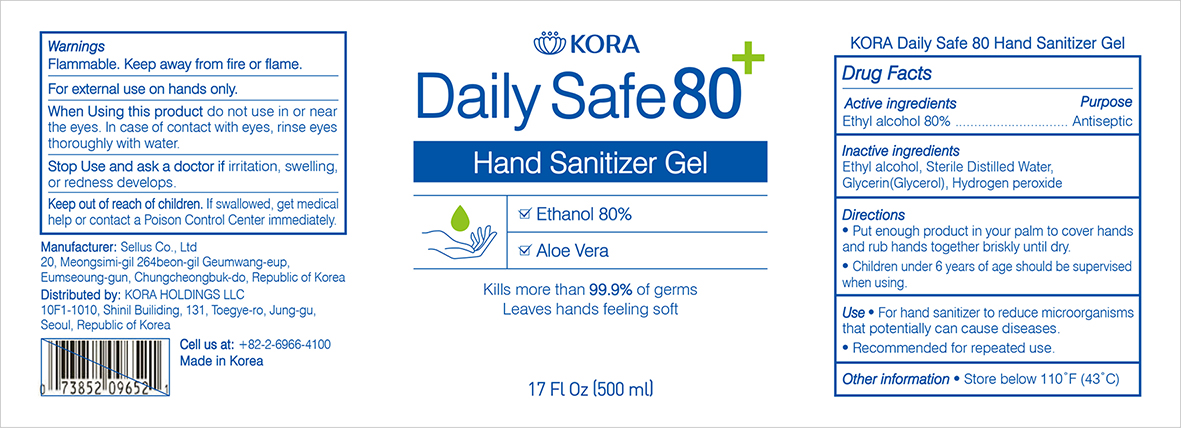 DRUG LABEL: KORA Daily Safe 80
NDC: 75504-180 | Form: GEL
Manufacturer: Kora Holdings LLC
Category: otc | Type: HUMAN OTC DRUG LABEL
Date: 20201215

ACTIVE INGREDIENTS: ALCOHOL 80 mL/100 mL
INACTIVE INGREDIENTS: GLYCERIN 1.45 mL/100 mL; HYDROGEN PEROXIDE 0.125 mL/100 mL; WATER

This is a hand sanitizer manufactured according to the Temporary Policy for Preparation of Certain Alcohol-Based Hand Sanitizer Products During the Public Health Emergency (CoViD-19); Guidance for Industry.

The hand sanitizer is manufactured using only the following United States Pharmacopoeia (USP) grade ingredients in the preparation of the product (percentage in final product formulation) consistent with World Health Organization (WHO) recommendations:

1. Alcohol (ethanol) (USP or Food Chemical Codex (FCC) grade) (80%, volume/volume (v/v)) in an aqueous solution denatured according to Alcohol and Tobacco Tax and Trade Bureau regulations in 27 CFR part 20.
2. Glycerol (1.45% v/v).
3. Hydrogen peroxide (0.125% v/v).
4. Sterile distilled water or boiled cold water.

The firm does not add other active or inactive ingredients. Different or additional ingredients may impact the quality and potency of the product.

Active Ingredient(s)

Alcohol 80% v/v. Purpose: Antiseptic

Purpose

Antiseptic, Hand Sanitizer

Use

For hand sanitizer to reduce microorganisms that potentially can cause diseases. Recommended for repeated use.

Use

-Put enough product in your palm to cover hands and rub hands together briskly until dry.

-Children under 6 years of age should be supervised when using.

Warnings

For external use on hands only. Flammable. Keep away from fire or flame

Do not use

- in or near the eyes. In case of contact with eyes, rinse eyes thoroughly with water.

When using this product do not use in or near the eyes. In case of contact with eyes, rinse eyes thoroughly with water.
Stop use and ask a doctor if irritation, swelling or redness develops.
Keep out of reach of children. If swallowed, get medical help or contact a Poison Control Center immediately.

Stop use and ask a doctor if irritation, swelling or redness develops.

Keep out of reach of children. If swallowed, get medical help or contact a Poison Control Center immediately.

Directions

- Put enough product in your palm to cover hands and rub hands together briskly until dry.
- Children under 6 years of age should be supervised when using.

Other information

- Store below 110°F (43°C)

Inactive ingredients

glycerin (Glycerol), hydrogen peroxide, Sterile Distilled Water

Package Label - Principal Display Panel

500 mL NDC: 75504-080-01